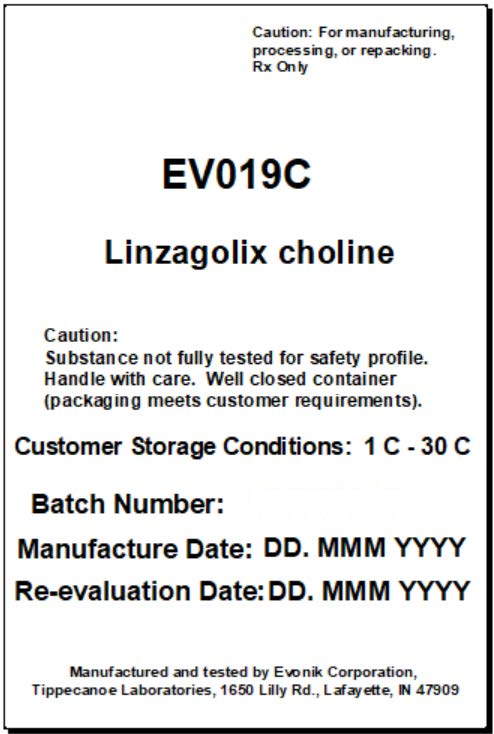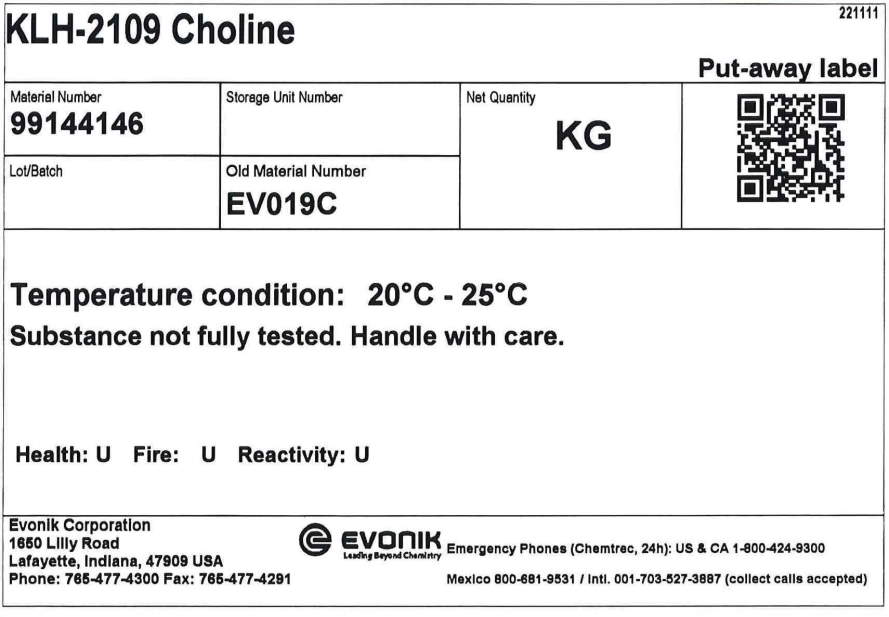 DRUG LABEL: KLH-2109 Choline
NDC: 62128-0395 | Form: POWDER
Manufacturer: Evonik Corporation
Category: other | Type: BULK INGREDIENT
Date: 20240208

ACTIVE INGREDIENTS: LINZAGOLIX CHOLINE 1 kg/1 kg

Linzagolix (KLH 2109) Choline, Kissei

Shipping NiceLabel Feb2024

Caution: For manufacturijg, processing or repacking. Rx only.

EV019C

Linzagolix Choline

Caution: Substance not fully tested for safety profile. Handle with care. Well closed container (packaging meets customer requirements).

Customer storage conditions: 1C - 30C

Batch number:

Manufacture date:

Re-evaluation date:

Manufactured and testesd by

Evonik Corporation

Tippecanoe Laboratories

1650 Lilly Rd

Lafayette, IN 47909

Warehouse KG (put-away) Label, ELMa, Dec 2022

Every drum will have a Warehouse (put-away) Kg label:

KLH-2109 Choline

Material number: 99144146

Storage unit number:

Lot/Batch:

Old Material number: EV019C

Net Quantity: xx.x KG

QR code

Temperature condition: 20°C - 25°C

Substance no fully tested. Handle with care.

Health: U

Fire: U

Reactivity: U

Evonik Corporation

1650 Lilly Road

Lafayette, Indiana, 47909 USA

Phone: 765-477-4300

Fax: 765-477-4291

Evonik: Leading Beyond Chemistry

Emergency Phone (Chemtrec, 24 h)

US & CA 1-800-424-9300

Mexico 800-681-9531

Intl 001-703-527-3887 (collect calls accepted)